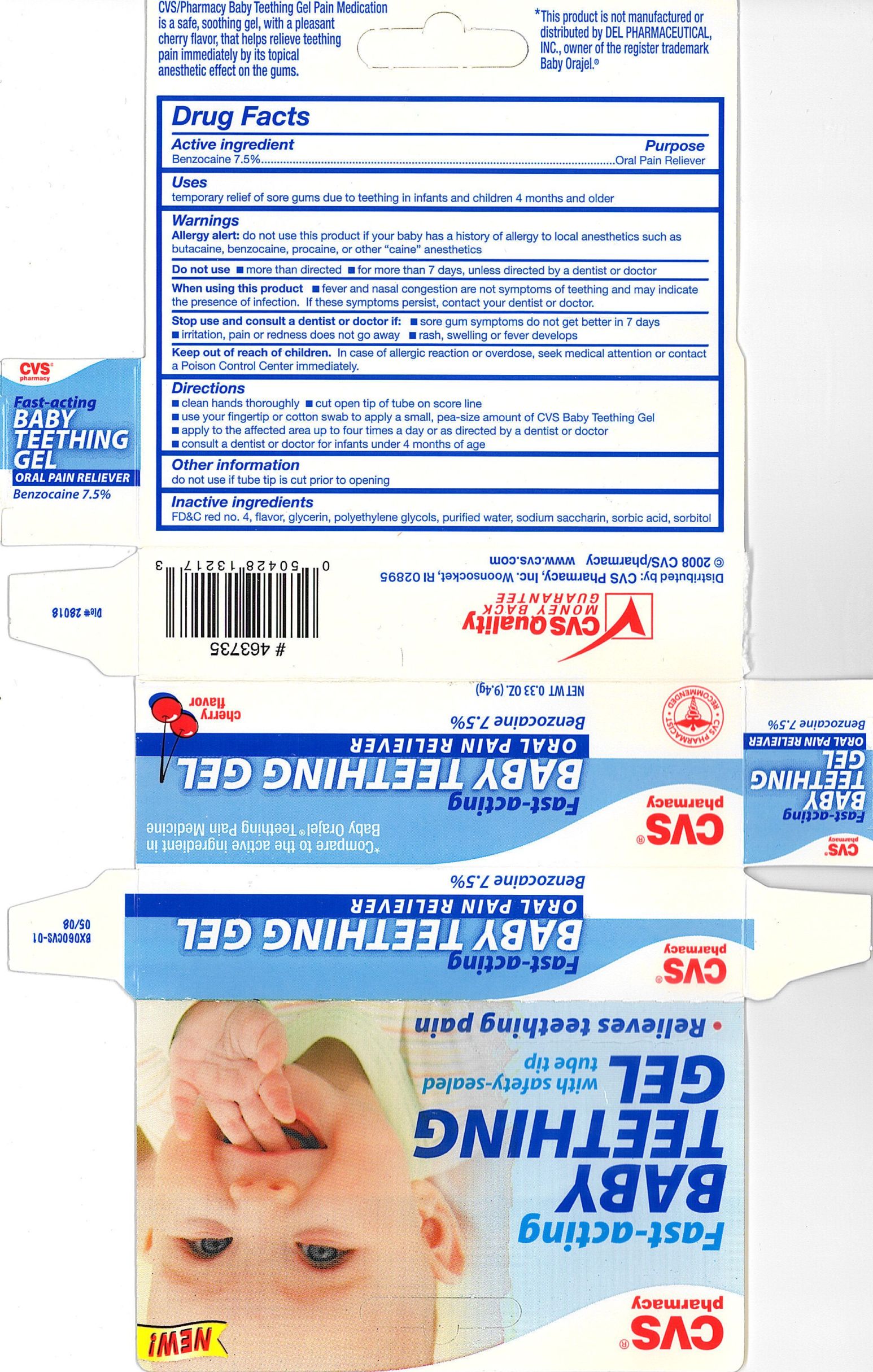 DRUG LABEL: CVS Fast Acting Baby Teething
NDC: 59779-829 | Form: GEL
Manufacturer: CVS Pharmacy
Category: otc | Type: HUMAN OTC DRUG LABEL
Date: 20100708

ACTIVE INGREDIENTS: BENZOCAINE 75 mg/1 g
INACTIVE INGREDIENTS: GLYCERIN; POLYETHYLENE GLYCOL 400; POLYETHYLENE GLYCOL 1450; SACCHARIN SODIUM; SORBITOL; FD&C RED NO. 4; WATER; SORBIC ACID

drug facts

Active ingredient Purpose
Benzocaine 7.5%............................................Oral Pain Reliever

Uses
- temporary relief of sore gums due to teething in infants and children 4 months and older

Keep out of reach of children. If case of allergic reaction or overdose, seek medical attention or contact
a Poison Control Center immediately.

Uses
- temporary relief of sore gums due to teething in infants and children 4 months or older
Other information- do not use if tube tip is cut prior to opening

Warnings
Allergy alert: do not use this product if your baby has a history of allergy to
local anesthetics such as butacaine, benzocaine, procaine, or other "caine" anesthetics
Do not use - more than directed - for more than 7 days, unless directed by a dentist or doctor
When using this product - fever and nasal congestion are not symptoms of teething
and may indicate the presence of infection. if these symptoms persist, contact your dentist or doctor.
Stop use and consult a dentist or doctor if:
- sore gum symptoms do not get better in 7 days
- irritation, pain or redness does not go away - rash, swelling or fever develops
Keep out of the reach of children. In case of allergic reaction or overdose,
seek medical attention or contact a Poison Control Center immediately.

Directions
- clean hands thoroughly - cut open tip of tube on score line
- use your fingertip or cotton swab to apply a small, pea-size amount of CVS Baby Teething Gel
- apply to the affected area up to four times a day or as directed by a dentist or doctor
- consult a dentist or doctor for infants under 4 months of age
Other information
do not use if tube tip is cut prior to opening

Inactive Ingredients
FD and C red no. 4, flavor, glycerin, propylene glycols, purified water, sodium saccharine, sorbic acid, sorbitol